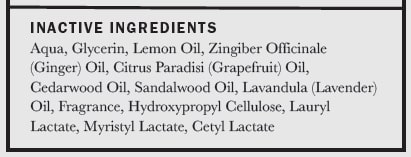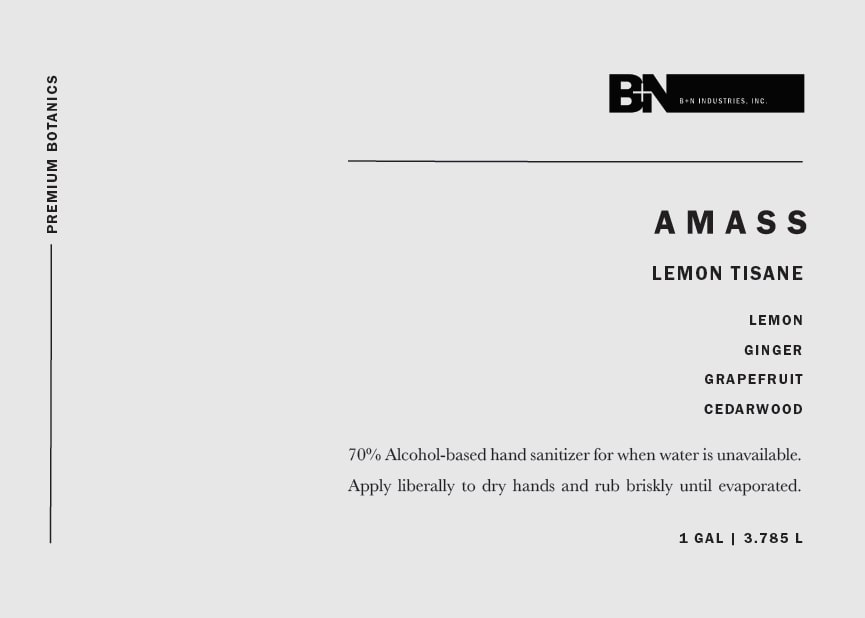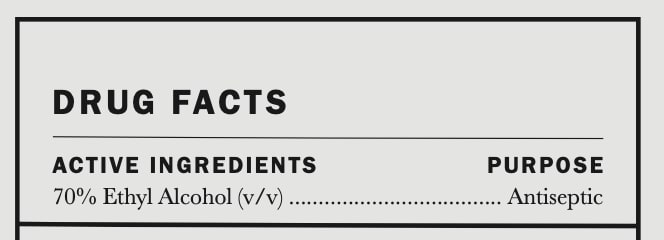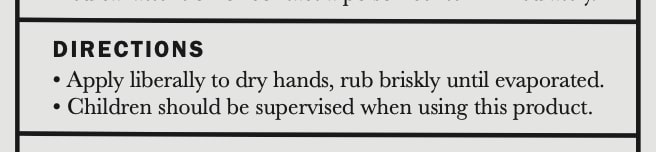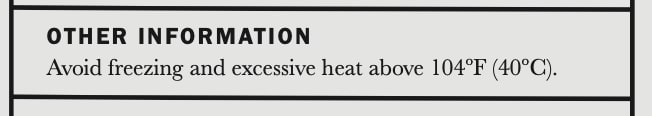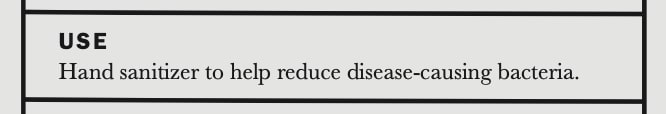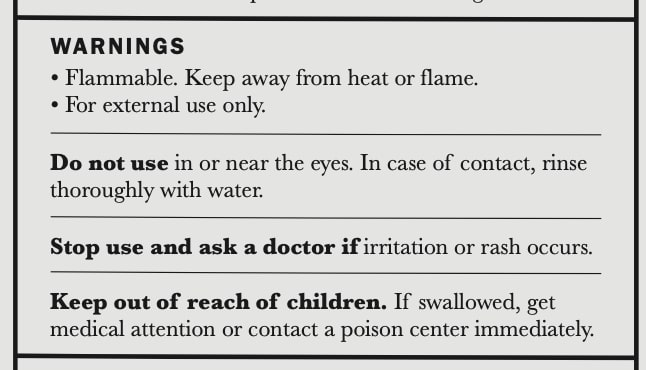 DRUG LABEL: AMASS Lemon Tisane Botanic Hand Sanitizer
NDC: 77419-4000 | Form: GEL
Manufacturer: AMASS Brands, Inc
Category: otc | Type: HUMAN OTC DRUG LABEL
Date: 20220101

ACTIVE INGREDIENTS: ALCOHOL 2.781975 L/3.785 L
INACTIVE INGREDIENTS: LAVENDER OIL; CEDRUS ATLANTICA BARK OIL; WATER; LAURYL LACTATE; LEMON OIL; GINGER OIL; GRAPEFRUIT OIL; SANDALWOOD OIL; LIMONENE, (+)-; HYDROXYPROPYL CELLULOSE (90000 WAMW); CETYL LACTATE; MYRISTYL LACTATE; GLYCEROL FORMAL; BENZYL BENZOATE; METHYL DIHYDROJASMONATE (SYNTHETIC)

Active Ingredients ......... Purpose
70% Ethyl Alcohol (v/v)........ Antiseptic

Do not use in or near the eyes. In case of contact, rinse thoroughly with water.

Keep out of reach of children. If swallowed, get medical attention or contact a poison center immediately.

USE
Hand sanitizer to help reduce disease-causing bacteria

Stop use and ask a doctor if irriation or rash occurs.

Directions
Apply liberally to dry hands, rub briskly until evaporated
Children should be supervised when using this product

OTHER INFORMATION
Avoid freezing and excessive heat above 104F (40C)

WARNINGS
Flammable. Keep away from heat or flame.
For external use only.
Do not use in or near the eyes. In case of contact, rinse thoroughly with water.
Stop use and ask a doctor if irritation or rash occurs.
Keep out of reach of children. IF swallowed, get medical attention or contact a poison center immediately.

DIRECTIONS
Apply liberally to dry hands, rub briskly until evaporated.
Children should be supervised when using this product

INACTIVE INGREDIENTS

Aqua, Glycerine, Lemon Oil, Zingiber Officinale (Ginger) Oil, Citrus Paradisi (Grapefruit) Oil, Cedarwood Oil, Sandalwood Oil, Lavandula (Lavender) Oil, Fragrance, Hydroxypropyl Cellulose, Lauryl Lactate, Myristyl Lactate, Cetyl Lactate

DIRECTIONS
Apply liberally to dry hands, rub briskly until evaporated.
Children should be supervised when using this product

WARNINGS
Flammable. Keep away from heat or flame.
For external use only.
Do not use in or near the eyes. In case of contact, rinse thoroughly with water.
Stop use and ask a doctor if irritation or rash occurs.
Keep out of reach of children. IF swallowed, get medical attention or contact a poison center immediately.

USE
Hand sanitizer to help reduce disease-causing bacteria.

PACKAGE LABEL

B+N logo
AMASS logo
LEMON TISANE
LEMON
GINGER
GRAPEFRUIT
CEDARWOOD
70% Alcohol-based hand sanitizer for when water is not available. Manufactured in Los Angeles, California.
1 gal | 3.785 l
---------------------------- Premium Botanics